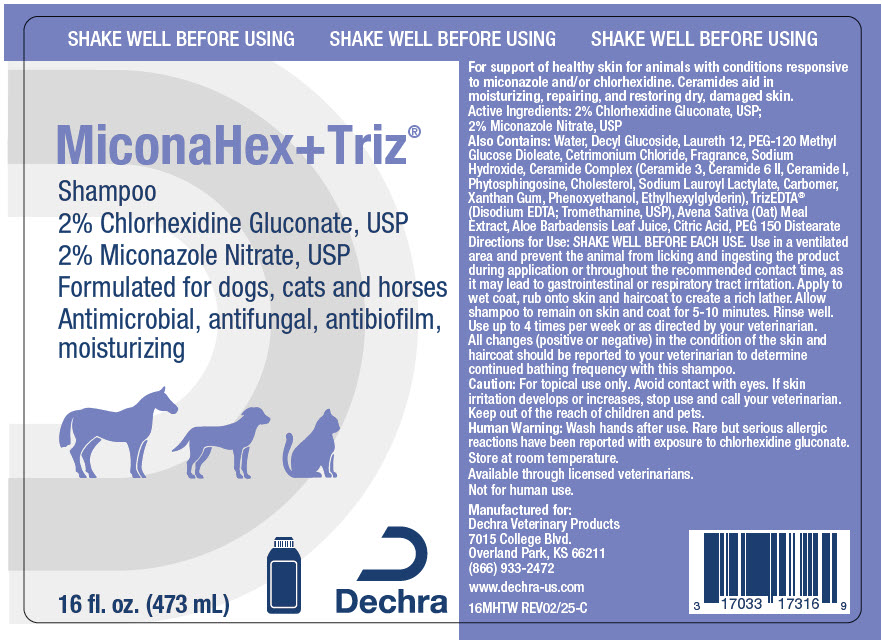 DRUG LABEL: MiconaHex plus Triz
NDC: 17033-173 | Form: SHAMPOO
Manufacturer: Dechra Veterinary Products
Category: animal | Type: OTC ANIMAL DRUG LABEL
Date: 20250609

ACTIVE INGREDIENTS: CHLORHEXIDINE GLUCONATE 20 mg/1 mL; MICONAZOLE NITRATE 20 mg/1 mL

MiconaHex + Triz® Shampoo

VETERINARY INDICATIONS

For support of healthy skin for animals with conditions responsive to miconazole and/or chlorhexidine. Ceramides aid in moisturizing, repairing, and restoring dry, damaged skin.

DESCRIPTION

Active Ingredients: 2% Chlorhexidine Gluconate, USP; 2% Miconazole Nitrate, USP

DESCRIPTION

Also Contains: Decyl Polyglucoside, Water, Laureth 12, Cetrimonium Chloride, PEG-120 Methyl Glucose Dioleate, Fragrance, Sodium Hydroxide, Ceramide Complex (Ceramide 3, Ceramide 6 II, Ceramide I, Phytosphingosine, Cholesterol, Sodium Lauroyl Lactylate, Carbomer, Xanthan Gum), TrizEDTA® (Disodium EDTA; Tromethamine, USP), Oatmeal Extract, Aloe Vera Gel, PEG 150 Distearate

DOSAGE AND ADMINISTRATION

Directions for Use: SHAKE WELL BEFORE EACH USE. Use in a ventilated area and prevent the animal from licking and ingesting the product during application or throughout the recommended contact time, as it may lead to gastrointestinal or respiratory tract irritation. Apply to wet coat, rub onto skin and haircoat to create a rich lather. Allow shampoo to remain on skin and coat for 5-10 minutes. Rinse well. Use up to 4 times per week or as directed by your veterinarian. All changes (positive or negative) in the condition of the skin and haircoat should be reported to your veterinarian to determine continued bathing frequency with this shampoo.

PRECAUTIONS

Caution: For topical use only. Avoid contact with eyes. If skin irritation develops or increases, stop use and call your veterinarian. Keep out of the reach of children and pets.

SAFE HANDLING WARNING

Human Warning: Wash hands after use. Rare but serious allergic reactions have been reported with exposure to chlorhexidine gluconate.

HOW SUPPLIED

STORAGE AND HANDLING

Store at room temperature.

Available through licensed veterinarians.

Not for human use.

Manufactured for: Dechra Veterinary Products
7015 College Blvd., Overland Park, KS 66211
866.933.2472
www.dechra-us.com

MHTW REV10/22

PRINCIPAL DISPLAY PANEL - 473 mL Bottle Label

SHAKE WELL BEFORE USING

MiconaHex+Triz®

Shampoo
2% Chlorhexidine Gluconate, USP
2% Miconazole Nitrate, USP

Formulated for dogs, cats and horses

Antimicrobial, antifungal, antibiofilm,
moisturizing

16 fl. oz. (473 mL)

Dechra